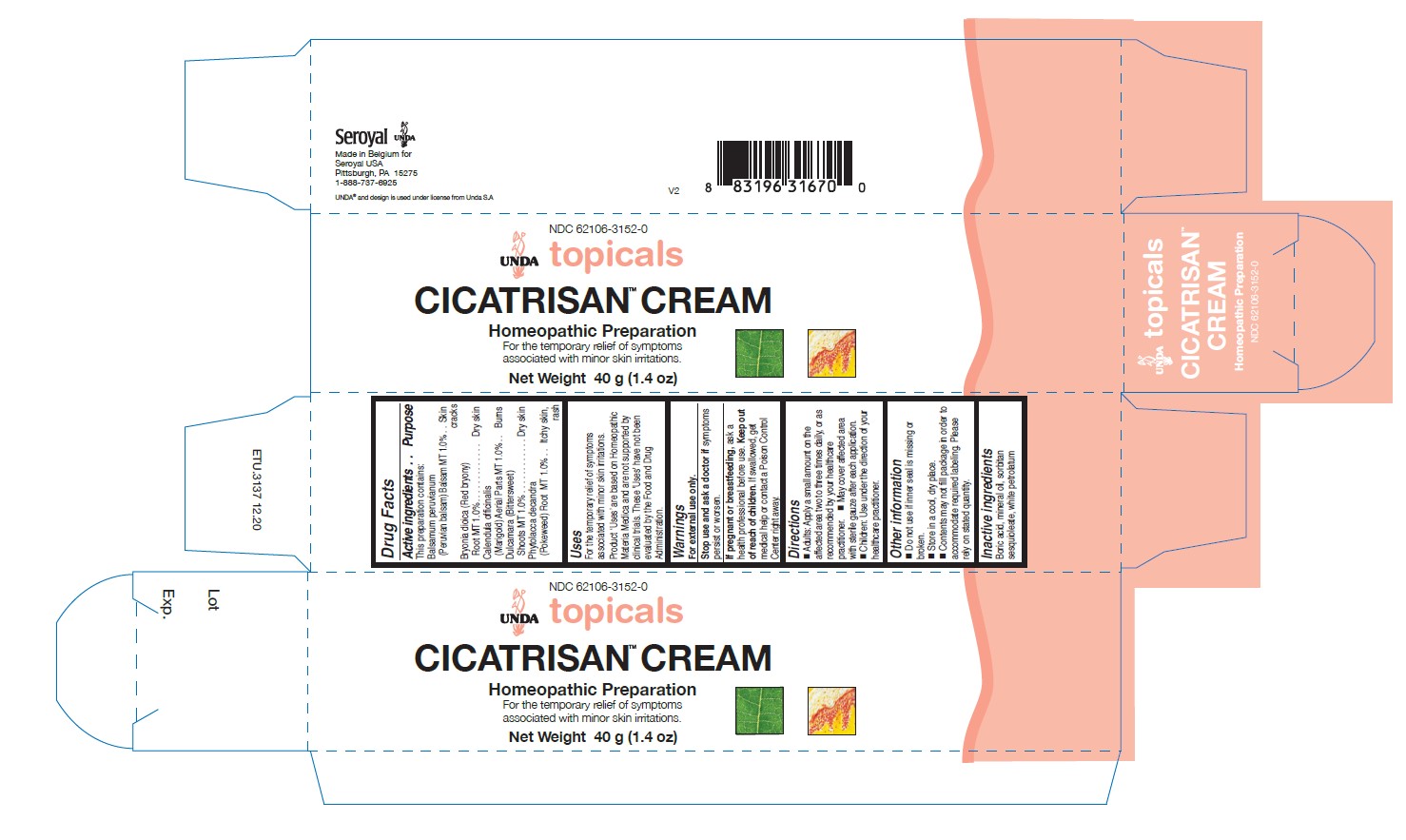 DRUG LABEL: CICATRISAN Cream
NDC: 62106-3152 | Form: CREAM
Manufacturer: Seroyal USA
Category: homeopathic | Type: HUMAN OTC DRUG LABEL
Date: 20210714

ACTIVE INGREDIENTS: BALSAM PERU 1 [hp_X]/40 g; BRYONIA DIOICA ROOT 1 [hp_X]/40 g; SOLANUM DULCAMARA TOP 1 [hp_X]/40 g; CALENDULA OFFICINALIS FLOWERING TOP 1 [hp_X]/40 g; PHYTOLACCA AMERICANA ROOT 1 [hp_X]/40 g
INACTIVE INGREDIENTS: BORIC ACID; PARAFFIN; MINERAL OIL; SORBITAN SESQUIOLEATE

CICATRISAN Cream

Active ingredients
This preparation contains:
Balsamum peruvianum
(Peruvian balsam) Balsam MT 1.0%
Bryonia dioica (Red bryony)
Root MT 1.0%
Calendula officinalis
(Marigold) Aerial Parts MT 1.0%
Dulcamara (Bittersweet)
Shoots MT 1.0%
Phytolacca decandra
(Pokeweed) Root MT 1.0%

Uses
For the temporary relief of symptoms
associated with minor skin irritations.

Warnings
For external use only.
Stop use and ask a doctor if symptoms
persist or worsen.
If pregnant or breastfeeding, ask a
health professional before use. Keep out
of reach of children. If swallowed, get
medical help or contact a Poison Control
Center right away.

Keep out of reach of children.

OVERDOSAGE

If swallowed, get medical help or contact a Poison
Control Center right away.

Inactive ingredients
Boric acid, mineral oil, sorbitan
sesquioleate, white petrolatum

Directions
Adults: Apply a small amount on the
affected area two to three times daily, or as
recommended by your healthcare
practitioner. May cover affected area with
sterile gauze after each application.
Children: Use under the direction of your
healthcare practitioner.

Uses
For the temporary relief of symptoms
associated with minor skin irritations.

Directions
Adults: Apply a small amount on the
affected area two to three times daily, or as
recommended by your healthcare
practitioner. May cover affected area with
sterile gauze after each application.
Children: Use under the direction of your
healthcare practitioner.

Other information
Do not use if inner seal is missing or
broken.
Store in a cool, dry place.

Contents may not fill package in order to
accommodate required labeling. Please
rely on stated quantity

PACKAGE LABEL

NDC 62106-3152-0

UNDA topicals

CICATRISAN CREAM

Homeopathic Preparation

For the temporary relief of symptoms
associated with minor skin irritations.

Net Weight 1.4 oz. (40 g)